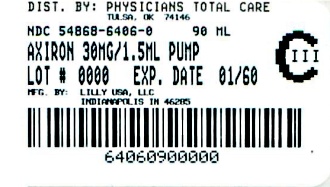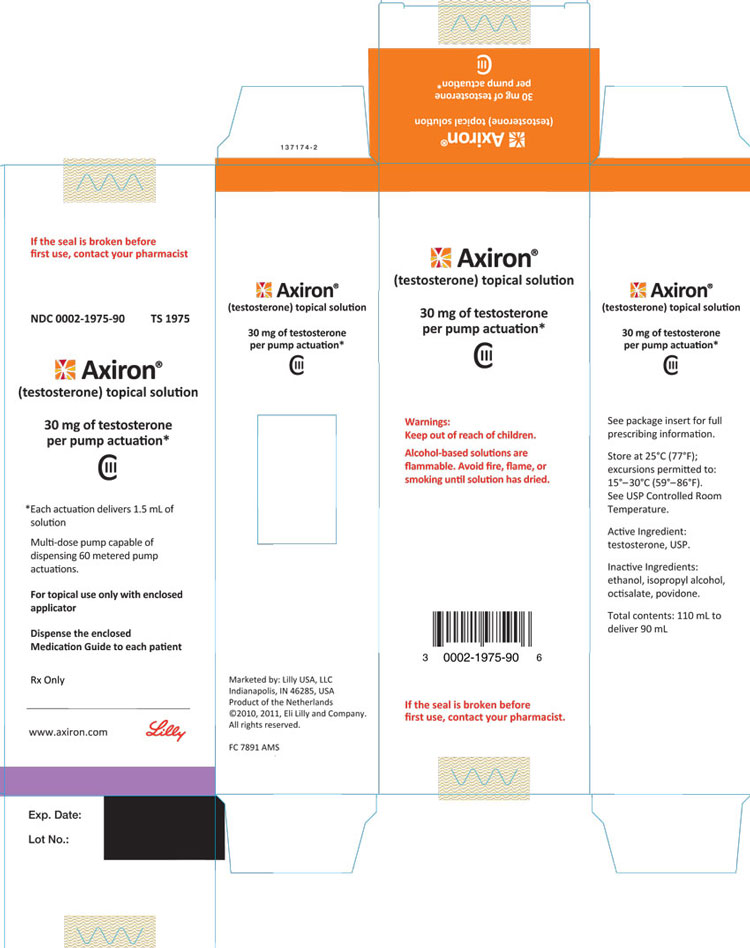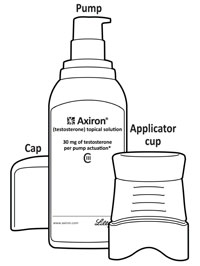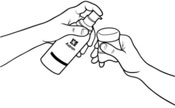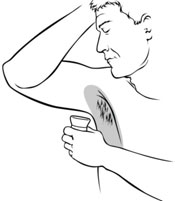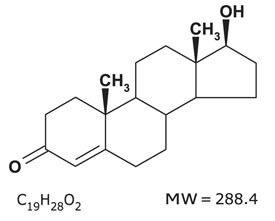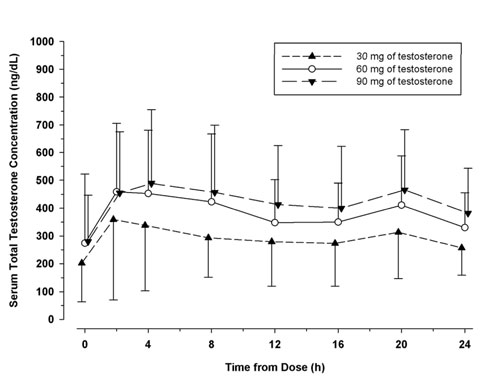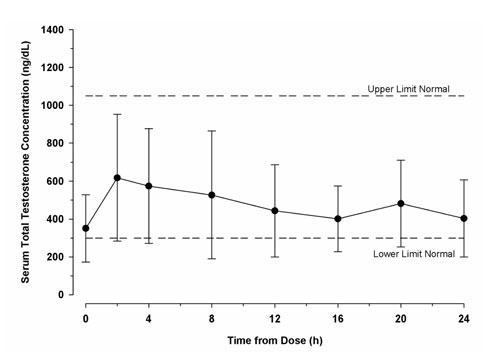 DRUG LABEL: AXIRON
                        
NDC: 54868-6406 | Form: SOLUTION
Manufacturer: Physicians Total Care, Inc.
Category: prescription | Type: HUMAN PRESCRIPTION DRUG LABEL
Date: 20131112
DEA Schedule: CIII

ACTIVE INGREDIENTS: TESTOSTERONE
 30 mg/1.5 mL
INACTIVE INGREDIENTS: OCTISALATE; POVIDONE; ISOPROPYL ALCOHOL; ALCOHOL

HIGHLIGHTS OF PRESCRIBING INFORMATION

These highlights do not include all the information needed to use AXIRON safely and effectively. See full prescribing information for AXIRON.
AXIRON (testosterone) topical solution, for topical use CIII
Initial U.S. Approval: 1953

WARNING: SECONDARY EXPOSURE TO TESTOSTERONE

- Virilization has been reported in children who were secondarily exposed to topical testosterone products (5.2)
- Children should avoid contact with unwashed or unclothed application sites in men using AXIRON (2.2, 5.2)
- Healthcare providers should advise patients to strictly adhere to recommended instructions for use (2.2, 5.2, 17)

1 INDICATIONS AND USAGE

AXIRON® is an androgen indicated for replacement therapy in males for conditions associated with a deficiency or absence of endogenous testosterone:

- Primary hypogonadism (congenital or acquired) (1)
- Hypogonadotropic hypogonadism (congenital or acquired) (1)

Important limitations of use: Safety and efficacy of AXIRON in males <18 years old have not been established (8.4)

2 DOSAGE AND ADMINISTRATION

- Starting AXIRON dose is 60 mg of testosterone (1 pump actuation of 30 mg of testosterone to each axilla), applied once daily, at the same time each morning. (2.1)
- Apply to clean, dry intact skin of the axilla, not to any other parts of the body including the abdomen or genitals (2.2)
- Dose adjustment: The dose of testosterone may be decreased from 60 mg (2 pump actuations) to 30 mg (1 pump actuation) or increased from 60 mg to 90 mg (3 pump actuations) or from 90 mg to 120 mg (4 pump actuations) based on the serum testosterone concentration from a single blood draw 2 – 8 hours after applying AXIRON and at least 14 days after starting treatment or following dose adjustment. (2.2)
- Patients should wash hands immediately with soap and water after applying AXIRON and cover the application site with clothing after the solution has dried. Wash the application site thoroughly with soap and water prior to any situation where skin-to-skin contact of the application site with another person is anticipated. (2.2)
- The application site and dose of AXIRON are not interchangeable with other topical testosterone products. (2.1)

3 DOSAGE FORMS AND STRENGTHS

AXIRON (testosterone) topical solution is available as a metered-dose pump. One pump actuation delivers 30 mg of testosterone. Each metered-dose pump is supplied with an applicator. (3)

4 CONTRAINDICATIONS

- Men with carcinoma of the breast or known or suspected carcinoma of the prostate (4, 5.1)
- Pregnant or breastfeeding women. Testosterone may cause fetal harm (4, 8.1, 8.3)

5 WARNINGS AND PRECAUTIONS

- Monitor patients with benign prostatic hyperplasia (BPH) for worsening of signs and symptoms of BPH (5.1)
- Avoid unintentional exposure of women or children to AXIRON. Secondary exposure to testosterone can produce signs of virilization. AXIRON should be discontinued until the cause of the virilization is identified (2.2, 5.2)
- Exogenous administration of testosterone may lead to azoospermia (5.5)
- Edema with or without congestive heart failure, may be a complication in patients with preexisting cardiac, renal, or hepatic disease (5.7).
- Sleep apnea may occur in those with risk factors (5.9)
- Monitor serum testosterone, prostate specific antigen (PSA), liver function, lipid concentrations, hematocrit and hemoglobin periodically (5.1, 5.3, 5.6, 5.10)
- AXIRON is flammable until dry (5.13)

6 ADVERSE REACTIONS

Most common adverse reactions (incidence >4%) are skin application site reactions, increased hematocrit, headache, diarrhea, vomiting, and increased serum PSA (6.1).

To report SUSPECTED ADVERSE REACTIONS, contact Eli Lilly and Company at 1-800-LillyRx (1-800-545-5979) or FDA at 1-800-FDA-1088 or www.fda.gov/medwatch.

7 DRUG INTERACTIONS

- Androgens may decrease blood glucose and insulin requirement in diabetic patients (7.1).
- Changes in anticoagulant activity may be seen with androgens. More frequent monitoring of International Normalized Ratio (INR) and prothrombin time is recommended (7.2).
- Use of testosterone with Adrenocorticotropic Hormone (ACTH) or corticosteroids may result in increased fluid retention. Use with caution, particularly in patients with cardiac, renal, or hepatic disease (7.3).

8 USE IN SPECIFIC POPULATIONS

- There are insufficient long-term safety data in geriatric patients using AXIRON to assess the potential risks of cardiovascular disease and prostate cancer (8.5).

FULL PRESCRIBING INFORMATION

WARNING: SECONDARY EXPOSURE TO TESTOSTERONE

- Virilization has been reported in children who were secondarily exposed to topical testosterone products [see Warnings and Precautions (5.2)].
- Children should avoid contact with unwashed or unclothed application sites in men using AXIRON [see Dosage and Administration (2.2) and Warnings and Precautions (5.2)].
- Healthcare providers should advise patients to strictly adhere to recommended instructions for use [see Dosage and Administration (2.2), Warnings and Precautions (5.2) and Patient Counseling Information (17)].

1 INDICATIONS AND USAGE

AXIRON is an androgen indicated for replacement therapy in males for conditions associated with a deficiency or absence of endogenous testosterone.

- Primary hypogonadism (congenital or acquired): testicular failure due to conditions such as cryptorchidism, bilateral torsion, orchitis, vanishing testis syndrome, orchiectomy, Klinefelter's syndrome, chemotherapy, or toxic damage from alcohol or heavy metals. These men usually have low serum testosterone concentrations and gonadotropins (FSH, LH) above the normal range.
- Hypogonadotropic hypogonadism (congenital or acquired): idiopathic gonadotropin or luteinizing hormone-releasing hormone (LHRH) deficiency or pituitary-hypothalamic injury from tumors, trauma, or radiation. These men have low testosterone serum concentrations but have gonadotropins in the normal or low range.

Important limitations of use — Safety and efficacy of AXIRON in males <18 years old have not been established [see Use in Specific Populations (8.4)].

2 DOSAGE AND ADMINISTRATION

2.1 Dosing and Dose Adjustment

The recommended starting dose of AXIRON (testosterone) topical solution is 60 mg of testosterone (2 pump actuations) applied once daily.

To ensure proper dosing, serum testosterone concentrations should be measured after initiation of therapy to ensure that the desired concentrations (300 ng/dL-1050 ng/dL) are achieved. The AXIRON dose can be adjusted based on the serum testosterone concentration from a single blood draw 2 – 8 hours after applying AXIRON and at least 14 days after starting treatment or following dose adjustment.

If the measured serum testosterone concentration is below 300 ng/dL, the daily testosterone dose may be increased from 60 mg (2 pump actuations) to 90 mg (3 pump actuations) or from 90 mg to 120 mg (4 pump actuations). If the serum testosterone concentration exceeds 1050 ng/dL, the daily testosterone dose should be decreased from 60 mg (2 pump actuations) to 30 mg (1 pump actuation) as instructed by a physician. If the serum testosterone concentration consistently exceeds 1050 ng/dL at the lowest daily dose of 30 mg (1 pump actuation), AXIRON therapy should be discontinued.

The application site and dose of AXIRON are not interchangeable with other topical testosterone products.

2.2 Administration Instructions

AXIRON is applied to the axilla, preferably at the same time each morning, to clean, dry, intact skin. Do not apply AXIRON to other parts of the body including to the scrotum, penis, abdomen, shoulders or upper arms. After applying the solution, the application site should be allowed to dry completely prior to dressing. Avoid fire, flames or smoking until the solution has dried since alcohol based products, including AXIRON, are flammable.

AXIRON is applied to the axilla using an applicator. When using AXIRON for the first time, patients should be instructed to prime the pump by depressing the pump three (3) times, discard any product dispensed directly into a basin, sink, or toilet and then wash the liquid away thoroughly. This priming should be done only prior to the first use of each pump. After priming, patients should completely depress the pump one time (one pump actuation) to dispense 30 mg of testosterone. To dispense the solution, position the nozzle over the applicator cup and carefully depress the pump fully once. Ensure that the liquid is directed into the cup. The cup should be filled with no more than 30 mg (1 pump actuation) of testosterone. Dosing that requires greater than one pump actuation must be applied in increments of 30 mg as is shown in Table 1.

Keeping the applicator upright, patients should place it up into the axilla and wipe steadily down and up into the axilla. If the solution drips or runs, it can be wiped back up with the applicator cup. The solution should not be rubbed into the skin with fingers or hand. The process is then repeated with application of 30 mg of testosterone (1 pump actuation) to the other axilla to achieve a total of 60 mg of testosterone applied. For patients prescribed the 90 mg dose of testosterone, the procedure is the same, but three applications are required. To dose 120 mg of testosterone, four applications are required alternating left and right for each application as shown in Table 1. When repeat application to the same axilla is required, the axilla should be allowed to dry completely before more AXIRON is applied.

After use, the applicator should be rinsed under room temperature, running water and then patted dry with a tissue. The applicator and cap are then replaced on the bottle for storage.

When deodorants or antiperspirants are used as part of a regular program for personal hygiene, they should not interfere with the efficacy of AXIRON in treating hypogonadism. If patients use an antiperspirant or deodorant (stick or roll-on) then it should be applied prior to the application of AXIRON to avoid contamination of the stick or roll-on product.

Patients should be advised to avoid swimming or washing the application site until two hours following application of AXIRON [see Clinical Pharmacology (12.3)].

To reduce the likelihood of interpersonal transfer of testosterone, the application site should always be washed prior to any skin-to-skin contact regardless of the length of time since application. [See Warnings and Precautions (5.2)].

Table 1: Application Technique
Daily Prescribed Dose of Testosterone | Number of Pump Actuations | Application
30 mg | 1 (once daily) | Apply once to one axilla only (left OR right)
60 mg | 2 (once daily) | Apply once to the left axilla and then apply once to the right axilla.
90 mg | 3 (once daily) | Apply once to the left and once to the right axilla, wait for the product to dry, and then apply once again to the left OR right axilla.
120 mg | 4 (once daily) | Apply once to the left and once to the right axilla, wait for the product to dry, and then apply once again to the left AND once to the right axilla.

Hands should be washed thoroughly with soap and water after AXIRON has been applied [see Warnings and Precautions (5.2)].

Strict adherence to the following precautions is advised in order to minimize the potential for secondary exposure to testosterone from AXIRON treated skin:

- Children and women should avoid contact with the unclothed or unwashed application sites on the skin of men using AXIRON.
- Patients should wash their hands immediately with soap and water after application of AXIRON.
- Patients should cover the application site(s) with clothing (e.g., a T-shirt) after the solution has dried.
- Prior to any situation in which direct skin-to-skin contact is anticipated, patients should wash the application site thoroughly with soap and water to remove any testosterone residue.
- In the event that unwashed or unclothed skin to which AXIRON has been applied comes in direct contact with the skin of another person, the general area of contact on the other person should be washed with soap and water as soon as possible.

While interpersonal testosterone transfer can occur with a T-shirt on, it has been shown that transfer can be substantially reduced by wearing a T-shirt and the majority of residual testosterone is removed from the skin surface by washing with soap and water.

3 DOSAGE FORMS AND STRENGTHS

AXIRON is a (testosterone) topical solution available as a metered-dose pump. One pump actuation delivers 30 mg of testosterone. Each metered-dose pump is supplied with an applicator.

4 CONTRAINDICATIONS

- AXIRON is contraindicated in men with carcinoma of the breast or known or suspected carcinoma of the prostate [see Warnings and Precaution (5.1)].
- AXIRON is contraindicated in women who are, or who may become pregnant, or who are breastfeeding. AXIRON may cause fetal harm when administered to a pregnant woman. AXIRON may cause serious adverse reactions in nursing infants. If a pregnant woman is exposed to AXIRON, she should be apprised of the potential hazard to the fetus. [See Use in Specific Populations (8.1, 8.3)].

5 WARNINGS AND PRECAUTIONS

5.1 Worsening of Benign Prostatic Hyperplasia and Potential Risk of Prostate Cancer

- Monitor patients with benign prostatic hyperplasia (BPH) for worsening of signs and symptoms of BPH.
- Patients treated with Androgens may be at increased risk for prostate cancer. Evaluate patients for prostate cancer prior to initiating treatment. It would be appropriate to reevaluate patients 3 to 6 months after initiation of treatment, and then in accordance with prostate cancer screening practices. [See Contraindications (4)].

5.2 Potential for Secondary Exposure to Testosterone

Cases of secondary exposure to testosterone in children and women have been reported with topical testosterone products applied to the abdomen or upper arms, including cases of secondary exposure resulting in virilization of children. Signs and symptoms have included enlargement of the penis or clitoris, development of pubic hair, increased erections and libido, aggressive behavior, and advanced bone age. In most cases, these signs and symptoms regressed with removal of the exposure to testosterone. In a few cases, however, enlarged genitalia did not fully return to age-appropriate normal size, and bone age remained modestly greater than chronological age. The risk of transfer was increased in some of these cases by not adhering to precautions for the appropriate use of the topical testosterone product. Children and women should avoid contact with unwashed or unclothed application sites in men using AXIRON [see Dosage and Administration (2.2), Use in Specific Populations (8.1) and Clinical Pharmacology (12.3)].

Inappropriate changes in genital size or development of pubic hair or libido in children, or changes in body hair distribution, significant increase in acne, or other signs of virilization in adult women should be brought to the attention of a physician and the possibility of secondary exposure to testosterone should also be brought to the attention of a physician. Testosterone therapy should be promptly discontinued at least until the cause of virilization has been identified. [See Dosage and Administration (2.2)].

5.3 Polycythemia

Increases in hematocrit, reflective of increases in red blood cell mass, may require lowering or discontinuation of testosterone. Check hematocrit prior to initiating testosterone treatment. It would be appropriate to re-evaluate the hematocrit 3 to 6 months after starting testosterone treatment, and then annually. If hematocrit becomes elevated, stop therapy until hematocrit decreases to an acceptable level. An increase in red blood cell mass may increase the risk of thromboembolic events.

5.4 Use in Women

Due to lack of controlled studies in women and potential virilizing effects, AXIRON is not indicated for use in women [see Contraindications (4) and Use in Specific Populations (8.1, 8.3)].

5.5 Potential for Adverse Effects on Spermatogenesis

At large doses of exogenous androgens, including AXIRON, spermatogenesis may be suppressed through feedback inhibition of pituitary follicle-stimulating hormone (FSH) which could possibly lead to adverse effects on semen parameters including sperm count.

5.6 Hepatic Adverse Effects

Prolonged use of high doses of orally active 17-alpha-alkyl androgens (methyltestosterone) has been associated with serious hepatic adverse effects (peliosis hepatitis, hepatic neoplasms, cholestatic hepatitis, and jaundice). Peliosis hepatitis can be a life-threatening or fatal complication. Long-term therapy with intramuscular testosterone enanthate has produced multiple hepatic adenomas. AXIRON is not known to cause these adverse effects.

5.7 Edema

Androgens, including AXIRON, may promote retention of sodium and water. Edema, with or without congestive heart failure, may be a serious complication in patients with pre-existing cardiac, renal, or hepatic disease [see Adverse Reactions (6)].

5.8 Gynecomastia

Gynecomastia may develop and may persist in patients being treated with androgens, including AXIRON, for hypogonadism.

5.9 Sleep Apnea

The treatment of hypogonadal men with testosterone may potentiate sleep apnea in some patients, especially those with risk factors such as obesity and chronic lung disease.

5.10 Lipids

Changes in serum lipid profile may require dose adjustment or discontinuation of testosterone therapy.

5.11 Hypercalcemia

Androgens, including AXIRON, should be used with caution in cancer patients at risk of hypercalcemia (and associated hypercalciuria). Regular monitoring of serum calcium concentrations is recommended in these patients.

5.12 Decreased Thyroxine-binding Globulin

Androgens, including AXIRON, may decrease concentrations of thyroxin-binding globulins, resulting in decreased total T4 serum concentration and increased resin uptake of T3 and T4. Free thyroid hormone concentration remain unchanged, however there is no clinical evidence of thyroid dysfunction.

5.13 Flammability

Alcohol based products, including AXIRON, are flammable; therefore, patients should be advised to avoid smoking, fire or flame until the AXIRON dose applied has dried.

6 ADVERSE REACTIONS

6.1 Clinical Trial Experience

Because clinical trials are conducted under widely varying conditions, adverse reaction rates observed in the clinical trials of a drug cannot be directly compared to rates in the clinical trials of another drug and may not reflect the rates observed in practice.

Clinical Trials in Hypogonadal Men

Table 2 shows the treatment emergent adverse reactions that were reported by either >4% of 155 patients in a 120 day, Phase 3 study or by >4% of 71 patients who continued to use AXIRON for up to 180 days. These data reflect the experience primarily with a testosterone dose of 60 mg, which was taken by all patients at the start of the study, and was the maintenance dose for 97 patients. However, the doses used varied from 30 mg to 120 mg.

Table 2: Adverse Reactions Seen With the Use of AXIRON in either the 120 Day Clinical Trial or in the Extension to 180 Days (>4%)
Event | 120 Days (155 Patients) | 180 Days (71 Patients)
Application Site Irritation | 11 (7%) | 6 (8%)
Application Site Erythema | 8 (5%) | 5 (7%)
Headache | 8 (5%) | 4 (6%)
Hematocrit Increased | 6 (4%) | 5 (7%)
Diarrhea | 4 (3%) | 3 (4%)
Vomiting | 4 (3%) | 3 (4%)
PSA Increased | 2 (1%) | 3 (4%)

Other less common adverse reactions reported by at least 2 patients in the 120 day trial included: application site edema, application site warmth, increased hemoglobin, hypertension, erythema (general), increased blood glucose, acne, nasopharyngitis, anger and anxiety. Other less common adverse reactions reported in fewer than 1% of patients in the 120 day trial included: asthenia, affect lability, folliculitis, increased lacrimation, breast tenderness, increased blood pressure, increased blood testosterone, neoplasm prostate and elevated red blood cell count.

During the 120 day trial one patient discontinued treatment because of affect lability/anger which was considered possibly related to AXIRON administration.

During the 120 day clinical trial there was an increase in mean PSA values of 0.13 ± 0.68 ng/mL from baseline. At the end of the 180 day extension clinical trial, there was an overall increase in mean PSA values of 0.1 ± 0.54 ng/mL.

Following the 120 day study, seventy-one (71) patients entered a two-month extension study with AXIRON. Two patients (3%) had adverse reactions that led to discontinuation of treatment during the period from Day 120 to Day 180. These reactions were: one patient with application site irritation (considered possibly related to AXIRON application) and one patient with dry skin and erythema, but not at the application site (considered not related to AXIRON administration) and application site erythema (considered possibly related to AXIRON administration).

No serious adverse reactions to AXIRON were reported during either the 120 day trial, or the extension to 180 days.

7 DRUG INTERACTIONS

7.1 Insulin

Changes in insulin sensitivity or glycemic control may occur in patients treated with androgens. In diabetic patients, the metabolic effects of androgens may decrease blood glucose and, therefore, insulin requirement.

7.2 Oral anticoagulants

Changes in anticoagulant activity may be seen with androgens. More frequent monitoring of INR and prothrombin time is recommended in patients taking anticoagulants, especially at the initiation and termination of androgen therapy.

7.3 Corticosteroids

The concurrent use of testosterone with ACTH or corticosteroids may result in increased fluid retention and should be monitored cautiously, particularly in patients with cardiac, renal or hepatic disease.

8 USE IN SPECIFIC POPULATIONS

8.1 Pregnancy

Pregnancy Category X [see Contraindications (4)] — AXIRON is contraindicated during pregnancy or in women who may become pregnant. Testosterone is teratogenic and may cause fetal harm. Exposure of a female fetus to androgens may result in varying degrees of virilization. If this drug is used during pregnancy, or if the patient becomes pregnant while taking this drug, the patient should be apprised of the potential hazard to a fetus.

8.3 Nursing Mothers

Although it is not known how much testosterone transfers into human milk, AXIRON is contraindicated in nursing women because of the potential for serious adverse reactions in nursing infants. Testosterone and other androgens may adversely affect lactation. [See Contraindications (4)].

8.4 Pediatric Use

Safety and efficacy of AXIRON has not been established in males <18 years of age. Improper use may result in acceleration of bone age and premature closure of epiphyses.

8.5 Geriatric Use

There have not been sufficient numbers of geriatric patients involved in controlled clinical studies utilizing AXIRON to determine whether efficacy in those over 65 years of age differs from younger patients. Of the 155 patients enrolled in the pivotal clinical study utilizing AXIRON, 21 were over 65 years of age. Additionally, there were insufficient long-term safety data in these patients utilizing AXIRON to assess a potential incremental risk of cardiovascular disease and prostate cancer.

8.6 Renal Impairment

No formal studies were conducted involving patients with renal impairment.

8.7 Hepatic Impairment

No formal studies were conducted involving patients with hepatic impairment.

8.8 Use in Men with Body Mass Index (BMI) >35 kg/m^2

Safety and efficacy of AXIRON in males with BMI >35 kg/m^2 has not been established.

9 DRUG ABUSE AND DEPENDENCE

9.1 Controlled Substance

AXIRON contains testosterone, a Schedule III controlled substance as defined by the Anabolic Steroids Control Act.

9.2 Abuse

Anabolic steroids, such as testosterone, are abused. Abuse is often associated with adverse physical and psychological effects.

9.3 Dependence

Although drug dependence is not documented in individuals using therapeutic doses of anabolic steroids for approved indications, dependence is observed in some individuals abusing high doses of anabolic steroids. In general, anabolic steroid dependence is characterized by any three of the following:

- Taking more drug than intended
- Continued drug use despite medical and social problems
- Significant time spent in obtaining adequate amounts of drug
- Desire for anabolic steroids when supplies of the drug are interrupted
- Difficulty in discontinuing use of the drug despite desires and attempts to do so
- Experience of withdrawal syndrome upon discontinuation of anabolic steroid use

10 OVERDOSAGE

No cases of overdose with AXIRON have been reported in clinical trials. There is one report of acute overdosage by injection of testosterone enanthate: testosterone concentrations of up to 11,400 ng/dL were implicated in a cerebrovascular accident. Treatment of overdosage would consist of discontinuation of AXIRON together with appropriate symptomatic and supportive care.

11 DESCRIPTION

AXIRON (testosterone) topical solution is a clear, colorless, single phase solution containing 30 mg of testosterone in 1.5 mL of AXIRON solution for topical administration through the axilla. The active pharmacologic ingredient in AXIRON is testosterone. Testosterone USP is a white to practically white crystalline powder chemically described as 17-beta hydroxyandrost-4-en-3-one. The structural formula is:

The inactive ingredients are ethanol, isopropyl alcohol, octisalate, and povidone.

12 CLINICAL PHARMACOLOGY

12.1 Mechanism of Action

Endogenous androgens, including testosterone and dihydrotestosterone (DHT), are responsible for the normal growth and development of the male sex organs and for maintenance of secondary sex characteristics. These effects include the growth and maturation of prostate, seminal vesicles, penis and scrotum; the development of male hair distribution, such as facial, pubic, chest and axillary hair; laryngeal enlargement, vocal cord thickening, alterations in body musculature and fat distribution. Testosterone and DHT are necessary for the normal development of secondary sex characteristics. Male hypogonadism results from insufficient secretion of testosterone and is characterized by low serum testosterone concentrations. Signs/symptoms associated with male hypogonadism include erectile dysfunction and decreased sexual desire, fatigue and loss of energy, mood depression, regression of secondary sexual characteristics and osteoporosis.

Male hypogonadism has two main etiologies. Primary hypogonadism is caused by defects of the gonads, such as Klinefelter's Syndrome or Leydig cell aplasia, whereas secondary hypogonadism is the failure of the hypothalamus (or pituitary) to produce sufficient gonadotropins (FSH, LH).

12.2 Pharmacodynamics

No specific pharmacodynamic studies were conducted using AXIRON.

12.3 Pharmacokinetics

Absorption — AXIRON delivers physiologic circulating testosterone that approximate normal concentration range (i.e., 300 - 1050 ng/dL) seen in healthy men following application to the axilla.

On the skin, the ethanol and isopropyl alcohol evaporate leaving testosterone and octisalate. The skin acts as a reservoir from which testosterone is released into the systemic circulation over time (see Figure 1). In general, steady-state serum concentrations are achieved by approximately 14 days of daily dosing.

Figure 1: Mean (±SD) Serum Testosterone Concentrations on Day 7 in Patients Following AXIRON Once-Daily Application of 30 mg, 60 mg, or 90 mg of Testosterone

When AXIRON treatment is discontinued after achieving steady-state, serum testosterone concentrations returned to their pretreatment concentrations by 7 – 10 days after the last application.

Distribution — Circulating testosterone is primarily bound in the serum to sex hormone-binding globulin (SHBG) and albumin. Approximately 40% of testosterone in plasma is bound to SHBG, 2% remains unbound (free) and the rest is bound to albumin and other proteins.

Metabolism —Testosterone is metabolized to various 17-keto steroids through two different pathways. The major active metabolites of testosterone are estradiol and dihydrotestosterone (DHT).

DHT concentration increased in parallel with testosterone concentration during AXIRON treatment. The mean steady-state DHT/T ratio remained within normal limits and ranged from 0.17 to 0.26 across all doses on Days 15, 60, and 120.

Excretion — There is considerable variation in the half-life of testosterone as reported in the literature, ranging from 10 to 100 minutes. About 90% of a dose of testosterone given intramuscularly is excreted in the urine as glucuronic and sulfuric acid conjugates of testosterone and its metabolites; about 6% of a dose is excreted in the feces, mostly in the unconjugated form. Inactivation of testosterone occurs primarily in the liver.

Potential for testosterone transfer: The potential for testosterone transfer from males dosed with AXIRON to healthy females was evaluated in a clinical study conducted with a 2% testosterone formulation. 10 males were treated with 60 mg (2 pump actuations) of testosterone in each axilla (the maximum testosterone dose of 120 mg). At 2 hours after the application of AXIRON to the males, the females rubbed their outer forearms for 15 minutes on the axilla of the males. The males had covered the application area with a T-shirt. Serum concentrations of testosterone were monitored in the female subjects for 72 hours after the transfer procedure. Study results show a 13% and 17% increase in testosterone exposure (AUC[0-24]) and maximum testosterone concentration (Cmax), respectively, compared to baseline in these females. In a prior clinical study conducted with a 1% testosterone formulation under similar study conditions, direct skin-to-skin transfer showed a 131% and 297% increase in testosterone exposure (AUC[0-72]) and maximum testosterone concentration (Cmax), respectively, compared to when men had covered the application area with a T-shirt.

In a clinical study conducted with a 2% testosterone formulation to evaluate the effect of washing on the residual amount of testosterone at the axilla, 10 healthy male subjects received 60 mg (2 pump actuations) of testosterone to each axilla (the maximum testosterone dose of 120 mg). Following 5 minutes of drying time, the left axilla was wiped with alcohol towelettes which were assayed for testosterone content. Subjects were required to shower with soap and water 30 minutes after application. The right axilla was then wiped with alcohol towelettes which were assayed for testosterone content. A mean (SD) of 3.1 (2.8) mg of residual testosterone (i.e., 92.6% reduction compared to when axilla was not washed) was recovered after washing this area with soap and water. [See Dosage and Administration (2.2) and Warnings and Precautions (5.2)].

Use of deodorants and anti-perspirants: In a parallel designed clinical study evaluating the effect of deodorants and antiperspirants in healthy premenopausal females dosed with AXIRON, each subject applied either a combined deodorant/antiperspirant spray (6 subjects) or stick (6 subjects) or a deodorant spray (6 subjects) to a single axilla 2 minutes before the application of 30 mg (1 pump actuation) of testosterone to the same axilla. A control group of 6 subjects only applied 30 mg (1 pump actuation) of testosterone to a single axilla. Blood samples were collected for 72 hours from all subjects following AXIRON administration. Although a decrease of up to 33% of testosterone exposure (AUC[0-72]) was observed when antiperspirants or deodorants are used 2 minutes prior to AXIRON application, underarm deodorant or antiperspirant spray or stick products may be used 2 minutes prior to AXIRON application as part of normal, consistent, and daily routine. [See Dosage and Administration (2.2), and Patient Counseling Information (17.4)].

Effect of showering/washing: In a parallel designed clinical study to evaluate the effect of washing on the testosterone systemic exposure, two groups of 6 healthy premenopausal female subjects were each dosed with 30 mg (1 pump actuation) of testosterone to a single axilla. The application sites of each group were washed with soap and water 2 hours or 6 hours after the application of AXIRON. A control group of 6 female subjects applied 30 mg (1 pump actuation) of testosterone to a single axilla and did not wash the application site. Blood samples were collected for 72 hours from all subjects following dosing with AXIRON. A decrease of up to 35% of testosterone exposure (AUC[0-72]) was observed when applications sites were washed 2 hours and 6 hours after AXIRON application. Patients should be advised to avoid swimming or washing the application site until 2 hours following application of AXIRON. [See Dosage and Administration (2.2) and Patient Counseling Information (17.4)].

13 NONCLINICAL TOXICOLOGY

13.1 Carcinogenesis, Mutagenesis, Impairment of Fertility

Testosterone has been tested by subcutaneous injection and implantation in mice and rats. In mice, the implant induced cervical-uterine tumors, which metastasized in some cases. There is suggestive evidence that injection of testosterone into some strains of female mice increases their susceptibility to hepatoma. Testosterone is also known to increase the number of tumors and decrease the degree of differentiation of chemically induced carcinomas of the liver in rats. Testosterone was negative in the in vitro Ames and in the in vivo mouse micronucleus assays. The administration of exogenous testosterone has been reported to suppress spermatogenesis in the rat, dog and non-human primates, which was reversible on cessation of the treatment.

14 CLINICAL STUDIES

14.1 Clinical Studies in Hypogonadal Men

AXIRON was evaluated in a multicenter, open label, 120-day trial that enrolled 155 hypogonadal men at 26 clinical research centers. The median age of subjects was 53 years with a range of 19 – 78 years. Of the 144 subjects whose race was recorded, 122 (84.7%) were Caucasian, 13 (9.0%) were Hispanic, 6 (4.2%) were African Americans, 1 (0.7%) was Asian and 2 (1.4%) had race recorded as “Other”.

Patients were instructed to apply AXIRON to unclothed, clean, dry, and unbroken skin. The solution was applied to the axillary area. Patients were not instructed to alter their normal grooming routine, e.g., shave under the arm.

During the initial AXIRON treatment period (Days 1-15) 143 patients were treated with 60 mg of testosterone daily. On Day 45 of the trial, patients were maintained at the same dose, or were titrated up or down, based on their 24 hour average serum testosterone concentration measured on Day 15. On Day 90 of the trial, patients were maintained at the same dose, or were titrated up or down, based on their 24 hour average serum testosterone concentration measured on Day 60.

On day 120, 75% of responding patients finished the study on the starting dose of 60 mg of testosterone, while 2% had been titrated to 30 mg, 17% had been titrated to 90 mg and 6% had been titrated to the 120 mg dose.

On day 60, 84.8% of subjects had total testosterone concentrations in the normal range. Of those who had sufficient data for analysis on day 120, 84.1%, had their average serum testosterone concentration in the normal range of 300 – 1050 ng/dL.

Table 3 summarizes the proportion of subjects having average testosterone concentrations within the normal range on Days 60 and 120.

Table 3: Proportion of subjects who had an average Serum Total Testosterone in the range 300 to 1050 ng/dL and completed 120 days of treatment (N=138a)
Evaluation Time | Statistics | Value
Baseline Testosterone | Mean (SD) | 194.6 ng/dL (92.9 ng/dL)
Day 15 | Normalb | 76.1%c
Day 15 | 95% CI | (69.0%, 83.2%)
Day 60 | Normalb | 84.8%
Day 60 | 95% CI | (78.8%, 90.8%)
Day 120 | Normalb | 84.1%
Day 120 | 95% CI | (77.9%, 90.2%)
a Three patients who withdrew from the study due to adverse reactions are included as treatment failures.
b Normal represents the percentage of patients with average testosterone concentration in the range of 300 – 1050 ng/dL.
c On Day 15, 72.2% of the 90 subjects in the US study population had an average serum testosterone in the range of 300 ng/dL – 1050 ng/dL.

Of the 135 patients who completed the 120 day treatment, 123 patients did so with no deviation from the protocol. By day 120, average serum testosterone concentration was within normal range for 67% of those who titrated down on the 30 mg dose, 89% of those on the 60 mg dose, 86% of those who titrated up to 90 mg and 70% of those who titrated up to the 120 mg dose. Table 4 below summarizes the testosterone concentration data in the patients who completed 120 days.

Table 4: Baseline-unadjusted Arithmetic Mean (±SD) Steady-State Serum Testosterone Concentrations on Days 15, 60 and 120 in Patients Who Completed 120 Days of Treatment
 | Dose of AXIRON
 | 30 mg | 60 mg | 90 mg | 120 mg | Overall
Day 15 | [N=0] | [N=135] | [N=0] | [N=0] | [N=135]
Cavg (ng/dL) | -- | 456 (±226) | -- | -- | 456 (±226)
Cmax (ng/dL) | -- | 744 (±502) | -- | -- | 744 (±502)
Day 60 | [N=1] | [N=105] | [N=29] | [N=0] | [N=135]
Cavg (ng/dL) | 343 (--) | 523 (±207) | 368 (±138) | -- | 488 (±204)
Cmax (ng/dL) | 491 (--) | 898 (±664) | 646 (±382) | -- | 840 (±620)
Day 120 | [N=3] | [N=97] | [N=25] | [N=10] | [N=135]
Cavg (ng/dL) | 493 (±239) | 506 (±175) | 415 (±165) | 390 (±160) | 480 (±177)
Cmax (ng/dL) | 779 (±416) | 839 (±436) | 664 (±336) | 658 (±353) | 792 (±417)

Figure 2 summarizes the pharmacokinetic profiles of total testosterone in patients completing 120 days of AXIRON treatment administered as 60 mg of testosterone for the initial 15 days followed by possible titration according to follow-up testosterone measurements.

Figure 2: Mean (± SD) Steady-State Serum Testosterone Concentrations on Day 120 (30, 60, 90 or 120 mg testosterone) in Patients Who Completed 120 Days (N=135) of AXIRON Once-Daily Treatment

16 HOW SUPPLIED/STORAGE AND HANDLING

16.1 How Supplied

AXIRON (testosterone) topical solution is available as a metered-dose pump containing 110 mL of solution. The pump is capable of dispensing 90 mL of solution in 60 metered pump actuations. One pump actuation delivers 30 mg of testosterone in 1.5 mL of solution. Each metered-dose pump is supplied with an applicator. Neither the bottle nor the applicator cup contains latex.

NDC 54868-6406-0

16.2 Storage and Handling

Keep AXIRON out of reach of children.

Store at 25°C (77°F). Excursions are permitted to 15°C to 30°C (59°F to 86°F). See USP Controlled Room Temperature.

Used AXIRON bottles and applicators should be discarded in household trash in a manner that prevents accidental exposure of children or pets.

17 PATIENT COUNSELING INFORMATION

See FDA-Approved Medication Guide.

Patients should be informed of the following information:

17.1 Use in Men with Known or Suspected Prostate or Breast Cancer

Men with known or suspected prostate or breast cancer should not use AXIRON. [See Contraindications (4) and Warnings and Precaution (5.1)].

17.2 Potential for Secondary Exposure to Testosterone and Steps to Prevent Secondary Exposure

Cases of secondary exposure to testosterone in children and women have been reported with topical testosterone products applied to the abdomen, shoulders or upper arms, including cases of secondary exposure resulting in virilization of children, with signs and symptoms including enlargement of the penis or clitoris, premature development of pubic hair, increased erections, aggressive behavior and advanced bone age. Inappropriate changes in genital size or premature development of pubic hair or libido in children, or changes in hair distribution, increase in acne, or other signs of testosterone effects in adult women should be brought to the attention of a physician and the possibility of secondary exposure to AXIRON also should be brought to the attention of a physician. AXIRON should be promptly discontinued at least until the cause of virilization is identified.

Strict adherence to the following precautions is advised in order to minimize the potential for secondary exposure to testosterone from AXIRON treated skin:

- AXIRON should only be applied to the axilla, not to any other part of the body.
- Children and women should avoid contact with the unwashed skin of the axilla or unclothed application sites of men where AXIRON has been applied.
- Patients should wash their hands immediately with soap and water after application of AXIRON.
- Patients should cover the axilla application site(s) with clothing (e.g., a shirt) after waiting 3 minutes for the solution to dry.
- Prior to any situation in which direct skin-to-skin contact of the axilla is anticipated, patients should wash the axilla to which AXIRON has been applied thoroughly with soap and water to remove any testosterone residue.
- In the event that unwashed or unclothed skin to which AXIRON has been applied comes in direct contact with the skin of another person, the general area of contact on the other person should be washed with soap and water as soon as possible.
  [See Dosage and Administration (2.2), Warnings and Precautions (5.2) and Clinical Pharmacology (12.3)].

17.3 Potential Adverse Reactions with Androgens

Patients should be informed that treatment with Androgens may lead to adverse reactions which include:

- Changes in urinary habits such as increased urination at night, trouble starting your urine stream, passing urine many times during the day, having an urge that you have to go to the bathroom right away, having urine accident, being unable to pass urine and having a weak urine flow.
- Breathing disturbances, including those associated with sleep, or excessive daytime sleepiness.
- Too frequent or persistent erections of the penis.
- Nausea, vomiting, changes in skin color, or ankle swelling.

17.4 Patients Should be Advised of these Application Instructions

- The pump should be primed by depressing it 3 times prior to its first use. No priming is needed with subsequent uses of that pump.
- AXIRON should NOT be applied to the scrotum, penis, abdomen, shoulders or upper arms.
- With testosterone doses greater than 60 mg, which require two applications of AXIRON to the same axilla, the product should be allowed to dry after the first application before the second is applied.
- AXIRON should be applied once daily at approximately the same time each day. AXIRON should be applied to clean, dry skin.
- Patients may use an antiperspirant or deodorant spray before applying AXIRON. If patients use a stick or roll-on antiperspirant or deodorant, then it should be applied prior to application of AXIRON to avoid contamination of the stick or roll-on product.
- Avoid swimming or washing the application site until two hours following application of AXIRON [see Dosage and Administration (2) and Clinical Pharmacology (12.3)].
- Avoid splashing in the eyes. In case of contact with eyes, flush thoroughly with water. If irritation persists, seek medical advice.

Literature revised December 2011

Marketed by: Lilly USA, LLC Indianapolis, IN 46285, USA

Copyright © 2010, 2011, Eli Lilly and Company. All rights reserved.

PV 8152 AMP

Distributed by:
Physicians Total Care, Inc.
Tulsa, OK 74146

Medication Guide

AXIRON® (AXE-e-RON) CIII

(testosterone) topical solution

Read this Medication Guide before you start using AXIRON and each time you get a refill. There may be new information. This information does not take the place of talking with your healthcare provider about your medical condition or treatment.

What is the most important information I should know about AXIRON?

AXIRON can transfer from your body to others. This can happen if other people come into contact with the area where the AXIRON was applied.

Signs of puberty that are not expected (for example, pubic hair) have happened in young children who were accidentally exposed to testosterone through skin to skin contact with men using topical testosterone products like AXIRON.

- Women and children should avoid contact with the unwashed or unclothed area where AXIRON has been applied. If a woman or child makes contact with the application area, the contact area on the woman or child should be washed well with soap and water right away.
- To lower the risk of transfer of AXIRON from your body to others, you should follow these important instructions:
  - Apply AXIRON only to your armpits.
  - Wash your hands right away with soap and water after applying AXIRON.
  - After the solution has dried, cover the application area with clothing. Keep the area covered until you have washed the application area well or have showered.
  - If you expect another person to have direct skin-to-skin contact with your armpits, first wash the application area well with soap and water.

Stop using AXIRON and call your healthcare provider right away if you see any signs and symptoms in a child or a woman that may have occurred through accidental exposure to AXIRON:

Signs and symptoms in children may include:

- enlarged penis or clitoris
- early development of pubic hair
- increased erections or sex drive
- aggressive behavior

Signs and symptoms in women may include:

- changes in body hair
- a large increase in acne

What is AXIRON?

AXIRON is a prescription medicine that contains testosterone. AXIRON is used to treat adult males who have low or no testosterone.

Your healthcare provider will test your blood before you start and while you are taking AXIRON.

It is not known if AXIRON is safe and effective in children younger than 18 years old. Improper use of AXIRON may affect bone growth in children.

AXIRON is a controlled substance (CIII) because it contains testosterone that can be a target for people who abuse prescription medicines. Keep your AXIRON in a safe place to protect it. Never give AXIRON to anyone else, even if they have the same symptoms you have. Selling or giving away this medicine may harm others and it is against the law.

AXIRON is not meant for use in women.

Who should not use AXIRON?

Do not use AXIRON if you:

- have breast cancer
- have or might have prostate cancer
- are pregnant or may become pregnant or are breast-feeding. AXIRON may harm your unborn or breast-feeding baby.

Women who are pregnant or who may become pregnant should avoid contact with the area of skin where AXIRON has been applied.

Talk to your healthcare provider before taking this medicine if you have any of the above conditions.

What should I tell my healthcare provider before using AXIRON?

Before you use AXIRON, tell your healthcare provider if you:

- have breast cancer
- have or might have prostate cancer
- have urinary problems due to an enlarged prostate
- have heart problems
- have kidney or liver problems
- have problems breathing while you sleep (sleep apnea)
- have any other medical conditions

Tell your healthcare provider about all of the medicines you take, including prescription and non-prescription medicines, vitamins, and herbal supplements.

Using AXIRON with other medicines can affect each other.

Especially tell your healthcare provider if you take:

- insulin
- medicines that decrease blood clotting
- corticosteroids

Know the medicines you take. Ask your healthcare provider or pharmacist for a list of all of your medicines if you are not sure. Keep a list of them and show it to your healthcare provider and pharmacist when you get a new medicine.

How should I use AXIRON?

- It is important that you apply AXIRON exactly as your healthcare provider tells you to.
- Your healthcare provider will tell you how much AXIRON to apply and when to apply it.
- Your healthcare provider may change your AXIRON dose. Do not change your AXIRON dose without talking to your healthcare provider.
- AXIRON is to be applied to the armpits only. Do not apply AXIRON to any other parts of your body such as your stomach area (abdomen), penis, scrotum, shoulders or upper arms.
- Do not apply AXIRON with your fingers or hands.
- Apply AXIRON at about the same time each morning. AXIRON should be applied after showering or bathing.
- Avoid swimming or bathing for at least 2 hours after you apply AXIRON.
- You can use an antiperspirant or deodorant before applying AXIRON. If you use antiperspirant or deodorant, then it should be applied at least 2 minutes before you apply AXIRON.
- AXIRON is flammable until dry. Let AXIRON dry before smoking or going near an open flame.
- Avoid splashing in the eyes. In case of contact with eyes, flush thoroughly with water. If irritation persists, seek medical advice.

Applying Axiron

AXIRON Figure 1

- Before using a new bottle of AXIRON for the first time, you will need to prime the pump. To prime the AXIRON pump gently push down on the pump 3 times. Do not use any AXIRON that came out while priming. Wash it down the sink to avoid accidental exposure to others. Your AXIRON pump is now ready to use.

- Use AXIRON exactly as your healthcare provider tells you to use it. Your healthcare provider will tell you the dose of AXIRON that is right for you. Apply your dose correctly by following the application instructions in the table below.

Find Your Dose as Prescribed by Your Doctor | Each application equals 1 depression of the pump.
30 mg | Apply 1 application once to one armpit only (left OR right).
60 mg | Apply 2 applications: one to the left armpit and then one to the right armpit.
90 mg | Apply 3 applications: one to the left and one to the right armpit, wait for the product to dry, and then apply again one to the left OR right armpit.
120 mg | Apply 4 applications: one to the left and one to the right armpit, wait for the product to dry, and then apply again one to the left AND one to the right armpit.

- Before applying AXIRON, make sure that your armpit is clean, dry and that there is no broken skin.

Figure 2

- Remove the cap and the applicator cup from the pump. Then, position the nozzle over the applicator cup and depress the pump gently (see Figure 2).

Figure 3

- To apply the AXIRON solution, keep the applicator upright, place it up into the armpit application site and wipe steadily down and up (see Figure 3).
- If AXIRON drips or runs, wipe it back up with the applicator cup. Do not rub in the solution with your fingers or hand once it has been applied.

- Let the application site dry completely before putting on a shirt.
- After you have finished applying AXIRON, rinse the applicator cup with room temperature running water, and then pat it dry with a tissue. Carefully replace the applicator cup and cap back onto the bottle and make sure you store the bottle safely.
- Clean up any spilled solution from surfaces such as the sink or floor to make sure others do not come into contact with it.
- Wash your hands with soap and water right away.

What are the possible side effects of AXIRON?

See also “What is the most important information I should know about AXIRON?”

AXIRON can cause serious side effects including:

- If you already have enlargement of your prostate gland your signs and symptoms can get worse while using AXIRON. This can include:
  - increased urination at night
  - trouble starting your urine stream
  - having to pass urine many times during the day
  - having an urge that you have to go to the bathroom right away
  - having a urine accident
  - being unable to pass urine or weak urine flow
- Possible increased risk of prostate cancer. Your healthcare provider should check you for prostate cancer or any other prostate problems before you start and while you use AXIRON.
- In large doses AXIRON may lower your sperm count.
- Swelling of your ankles, feet, or body.
- Enlarged or painful breasts.
- Problems breathing while you sleep (sleep apnea).
- Blood clots in the legs. This can include pain, swelling or redness of your legs.

Call your healthcare provider right away if you have any of the serious side effects listed above.

The most common side effects of AXIRON include:

- skin redness or irritation where AXIRON is applied
- increased red blood cell count
- headache
- diarrhea
- vomiting
- increase in blood level of Prostate Specific Antigen (a test used to screen for prostate cancer)

Other side effects include more erections than are normal for you or erections that last a long time.

Tell your healthcare provider if you have any side effect that bothers you or that does not go away.

These are not all the possible side effects of AXIRON. For more information, ask your healthcare provider or pharmacist.

Call your doctor for medical advice about side effects. You may report side effects to FDA at 1-800-FDA-1088.

How should I store AXIRON?

Store AXIRON at 15°C to 30°C (59°F to 86°F)

When it is time to throw away the bottle, safely throw away all parts of the AXIRON dispenser including bottle applicator cup and cap. Be careful to prevent accidental exposure of children or pets.

Keep AXIRON away from fire.

General information about AXIRON

Medicines are sometimes prescribed for purposes other than those listed in a Medication Guide. Do not use AXIRON for a condition for which it was not prescribed. Do not give AXIRON to other people, even if they have the same symptoms you have. It may harm them.

This Medication Guide summarizes the most important information about AXIRON. If you would like more information, talk to your healthcare provider. You can ask your pharmacist or healthcare provider for information about AXIRON that is written for health professionals.

For more information, go to www.axiron.com or call 1-800-545-5979.

What are the ingredients in AXIRON?

Active ingredient: testosterone.

Inactive ingredients: ethanol, isopropyl alcohol, octisalate, and povidone.

The bottle or applicator cup does not contain latex.

This Medication Guide has been approved by the U.S. Food and Drug Administration.

Literature issued November 2010

Marketed by: Lilly USA, LLC Indianapolis, IN 46285, USA

PV 8161 AMP

PACKAGE LABEL – Axiron Bottle 30mg 1ct

If the seal is broken before first use, contact your pharmacist

NDC 0002-1975-90

TS 1975

Axiron®

(testosterone) topical solution

30 mg of testosterone per pump actuation*

CIII

*Each actuation delivers 1.5 mL of solution

Multi-dose pump capable of dispensing 60 metered pump actuations.

For topical use only with enclosed applicator

Dispense the enclosed Medication Guide to each patient

Rx Only

www.axiron.com

Lilly